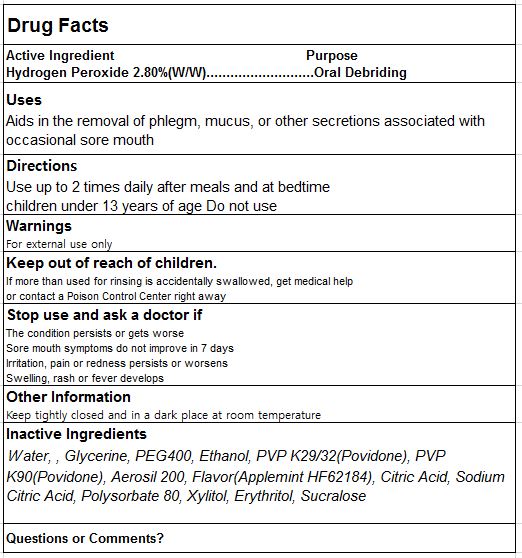 DRUG LABEL: Luzen Whitening Gel
NDC: 70812-010 | Form: GEL
Manufacturer: BIOSTECH CO., LTD.
Category: otc | Type: HUMAN OTC DRUG LABEL
Date: 20201222

ACTIVE INGREDIENTS: HYDROGEN PEROXIDE 2.8 g/100 g
INACTIVE INGREDIENTS: WATER; GLYCERIN; ALCOHOL; SILICON DIOXIDE; CITRIC ACID MONOHYDRATE; POLYSORBATE 80; XYLITOL; ERYTHRITOL; SUCRALOSE

ACTIVE INGREDIENT

hyeroge peroxide

DOSAGE AND ADMINISTRATION

for external use only

PURPOSE

oral debriding

INDICATIONS AND USAGE

Aids in the removal of phlegm, mucus, or other secretions associated with occasional sore mouth

INACTIVE INGREDIENT

water, glycerin, peg400, ethanol, pvp k29/32(povidone), pvp k90(povidone), aerosil 200, flavor, etc

Keep out of children

WARNINGS

for external use only

keep out of reach children